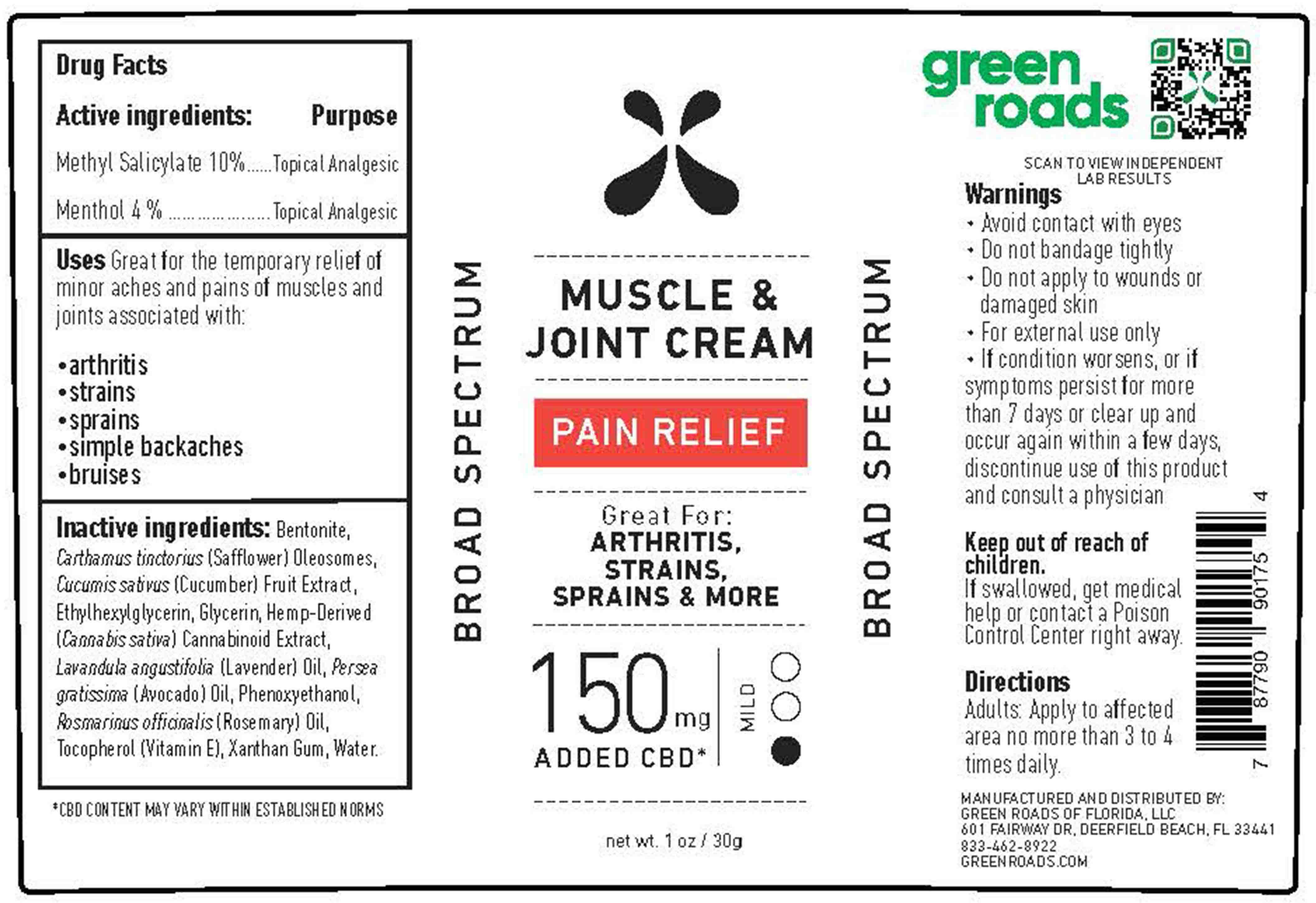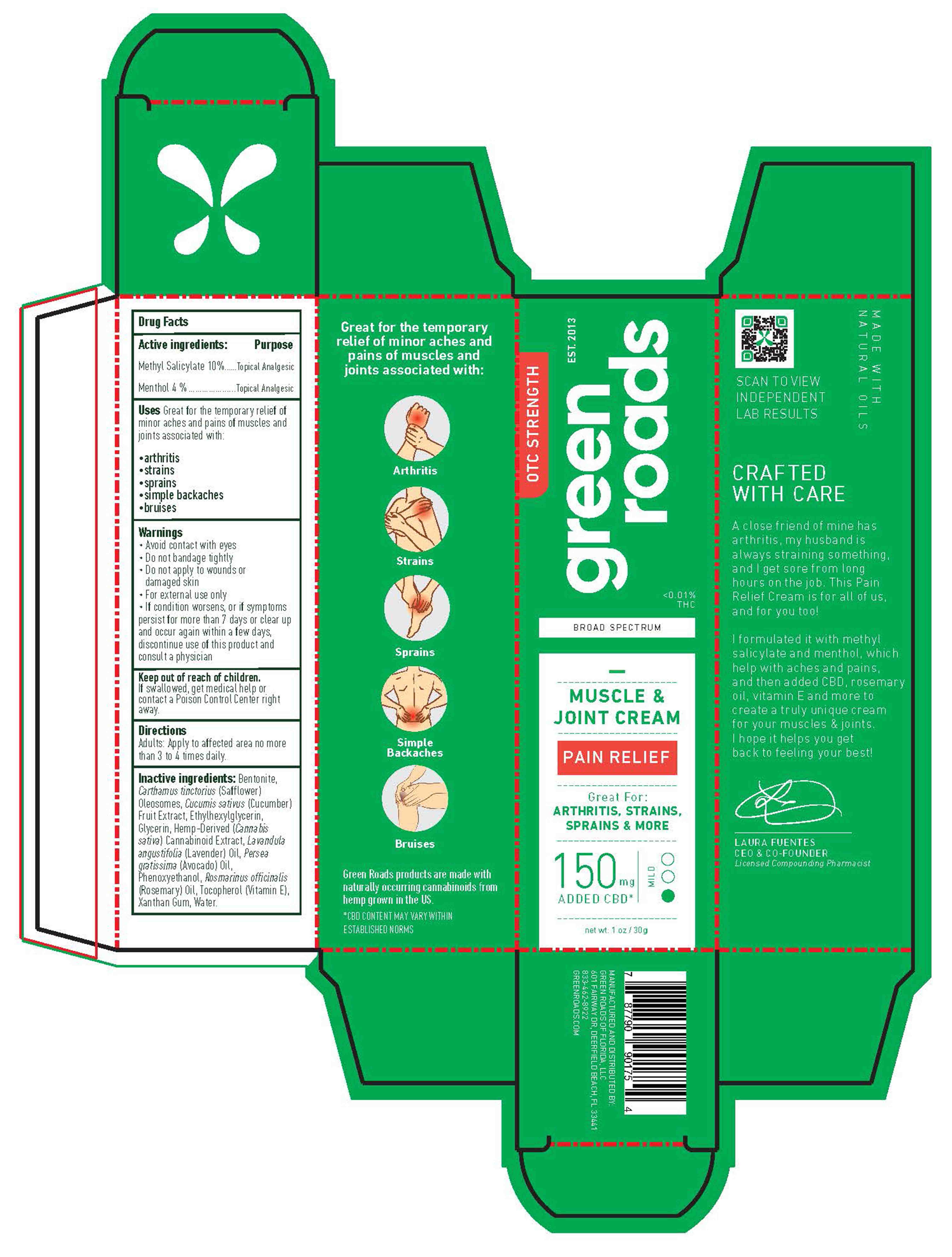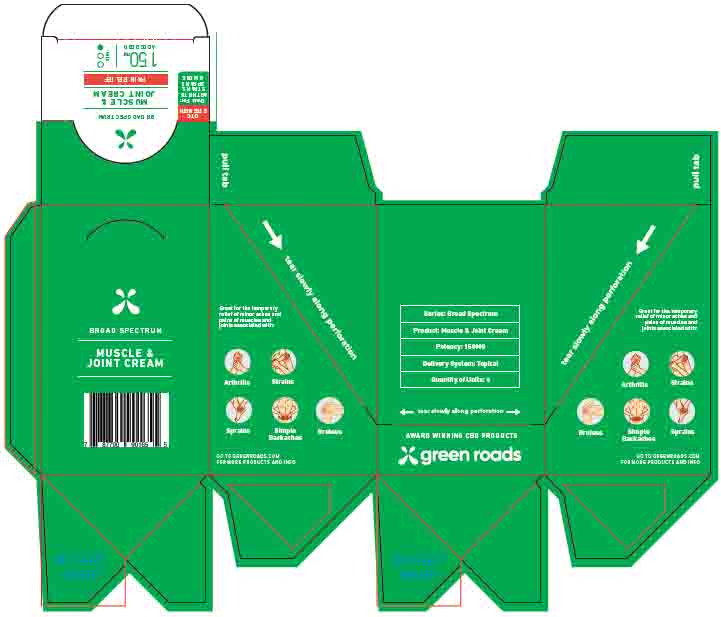 DRUG LABEL: Muscle and Joint pain relief GR Isolate 150 mg
NDC: 78232-004 | Form: CREAM
Manufacturer: Clarity Labs LLC
Category: otc | Type: HUMAN OTC DRUG LABEL
Date: 20211128

ACTIVE INGREDIENTS: MENTHOL 4 g/100 g; METHYL SALICYLATE 10 g/100 g
INACTIVE INGREDIENTS: LAVENDER OIL 0.83 g/100 g; CUCUMBER 0.83 g/100 g; WATER 58.576 g/100 g; CARTHAMUS TINCTORIUS (SAFFLOWER) OLEOSOMES 12.5 g/100 g; .ALPHA.-TOCOPHEROL 0.83 g/100 g; ETHYLHEXYLGLYCERIN 0.1 g/100 g; PHENOXYETHANOL 0.9 g/100 g; AVOCADO OIL 5 g/100 g; CANNABIDIOL 0.604 g/100 g; BENTONITE 5 g/100 g; CHAMOMILE 0.83 g/100 g

Muscle and Joint pain relief Mild 150 mg 1 Oz/30 g

This Pain Relief Cream has been formulated with methyl salicylate and menthol to help with aches and pains, and then added CBD, rosemary oil, vitamin E and more to create a truly unique cream for the wellbeing of muscles and joints.

Active Ingredients

Methyl Salicylate 10% w/w. Purpose: Topical Analgesic

Menthol 4% w/w. Purpose: Topical Analgesic

Purpose

Topical Analgesic, pain relief cream

Use

Pain relief cream to help reduce minor aches and pains of muscles and joints associated with: arthritis, strains, sprains, simple backaches, and bruises.

Do not use

in children

on open skin wounds

WHEN USING

This product is for external use only.

When using this product keep out of eyes, ears, and mouth. In case of contact with eyes, rinse eyes thoroughly with water.

Do not bandage tightly when applying this product.

Do not apply this product more than 4 times per day.

Stop use and ask a doctor if irritation or rash occurs. If condition worsens, or if symptoms persist for more than 7 days or clear up and occur again within a few days, discontinue use of this product and consult a physician.

Keep out of reach of children. If swallowed, get medical help or contact a Poison Control Center right away.

Stop use and ask a doctor if irritation or rash occurs. If condition worsens, or if symptoms persist for more than 7 days or clear up and occur again within a few days, discontinue use of this product, and consult a physician.

Keep out of reach of children. If swallowed, get medical help, or contact a Poison Control Center right away.

Directions

This product is for external use only.

Place enough on one hand to cover the affected area and rub the area accordingly.

Apply to affected area no more than 3 to 4 times daily.

Other information

Store between 15-30C (59-86F)

Avoid freezing and excessive heat above 40C (104F)

Inactive Ingredients

Bentonite, Carthamus tinctorius Oleosomes, Cucumis sativus Fruit Extract, Ethylhexylglycerin, Glycerin, Hemp Derived Cannabinoid Extract, Lavandula angustifolia Oil, Persea gratissima Oil, Phenoxyethanol, Rosmarinus officinalis Oil, Tocopherol, Xanthan Gum, Water.

Manufacturing and Distributors information

MANUFACTURED AND DISTRIBUTED BY:

GREEN ROADS OF FLORIDA, LLC
601 FAIRWAY DR, DEERFIELD BEACH, FL 33441

833-462-8922
GREENROADS.COM

WARNINGS

Avoid contact with eyes

Do not bandage tightly

Do not apply to wounds or damaged skin

For external use only

Design and Label of BOX

Tube Label

Package Label Outer Box IFC

IFC Individual Folding Carton

Most outer BOX

Big Container BOX